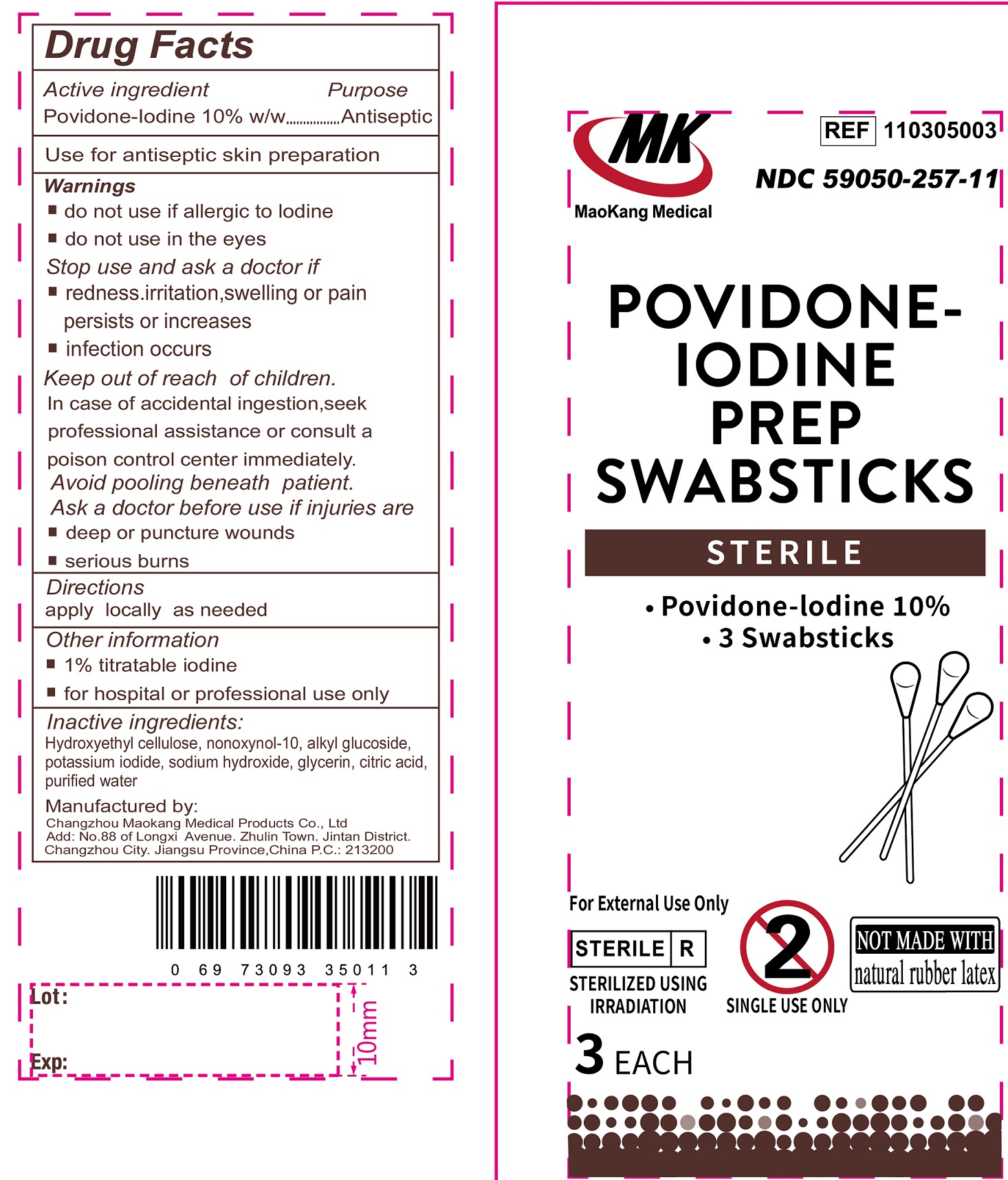 DRUG LABEL: MK Povidone-Iodine Swabstick Sterile
NDC: 59050-257 | Form: LIQUID
Manufacturer: Changzhou Maokang Medical Products Co., Ltd
Category: otc | Type: HUMAN OTC DRUG LABEL
Date: 20231109

ACTIVE INGREDIENTS: POVIDONE-IODINE 100 mg/1 mL
INACTIVE INGREDIENTS: HYDROXYETHYL CELLULOSE, UNSPECIFIED; NONOXYNOL-10; POTASSIUM IODIDE; SODIUM HYDROXIDE; GLYCERIN; CITRIC ACID MONOHYDRATE; WATER

MK Povidone-Iodine Swabstick Sterile

Active ingredient

Povidone-Iodine 10% w/w

Purpose

Antiseptic

Use

for antiseptic skin preparation

Warnings

Do not use

- if allergic to Iodine
- do not use in the eye

Stop use and ask a doctor if

- redness, irritation, swelling or pain persists or increases
- Infection occurs

Keep out of reach of children.

In case of accidental ingestion. seek professional assistance or consult a poison control center immediately. Avoid pooling beneath patient.

Ask a doctor before use if injuries are.

- deep or puncture wounds
- serious burns

Directions

apply locally as needed.

Other information

- 1% titratable iodine
- for hospital or prodessional use only

Inactive ingredients:

Hydroxyethyl cellulose, nonexynol-10, alkyl glucoside, potassium iodide, sodium hydroxide, glycerin, citric acid, purified water.